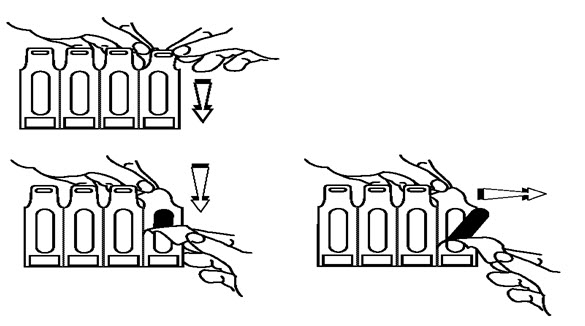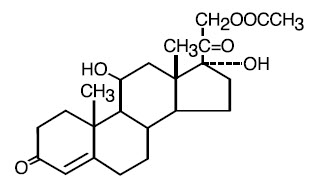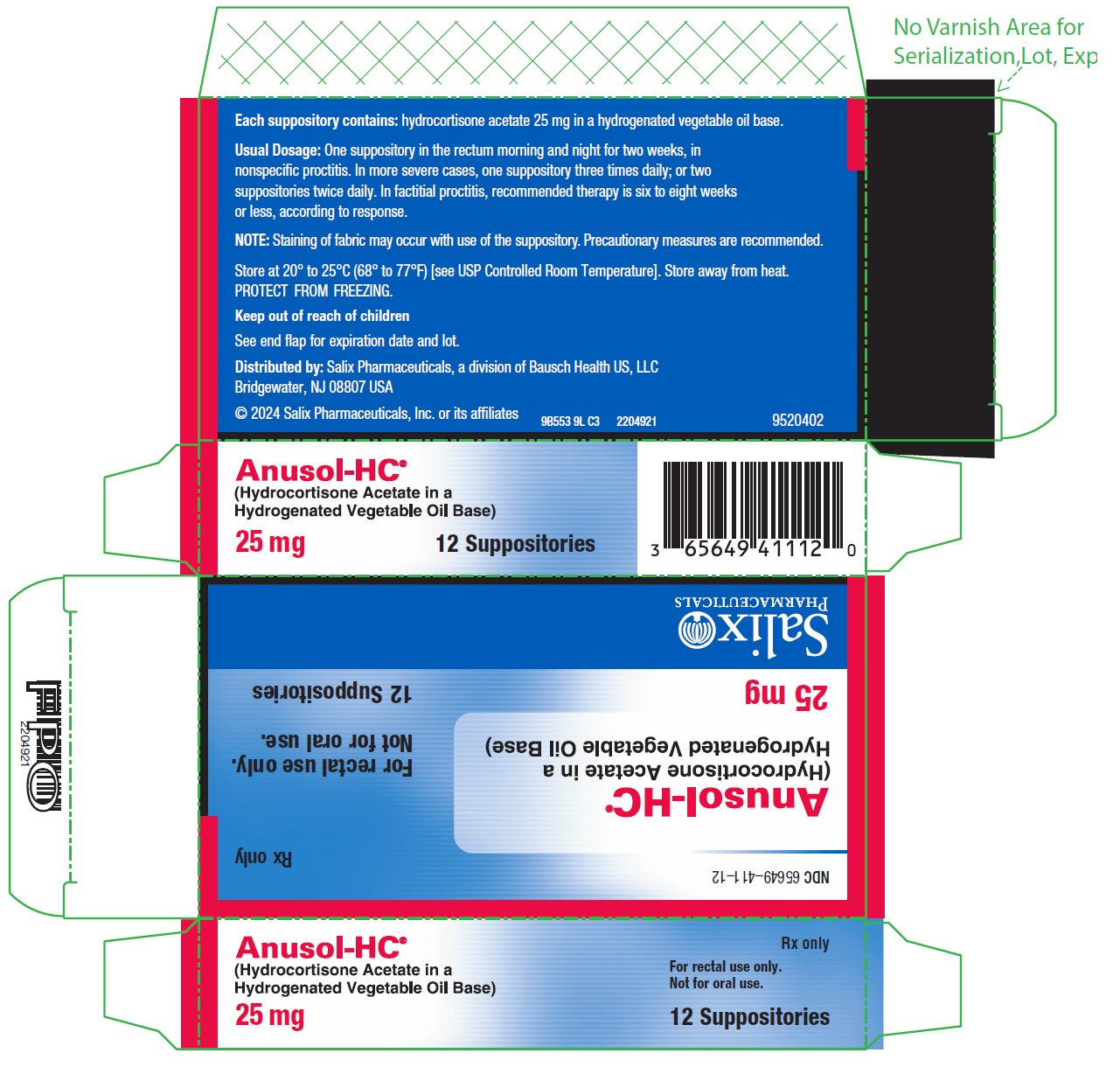 DRUG LABEL: Anusol HC
NDC: 65649-411 | Form: SUPPOSITORY
Manufacturer: Salix Pharmaceuticals, Inc
Category: prescription | Type: HUMAN PRESCRIPTION DRUG LABEL
Date: 20240701

ACTIVE INGREDIENTS: HYDROCORTISONE ACETATE 25 mg/1 1
INACTIVE INGREDIENTS: HYDROGENATED PALM OIL; SILICON DIOXIDE; BUTYLATED HYDROXYANISOLE

Anusol-HC® Hydrocortisone Acetate Rectal Suppositories, 25 mg
Rx only

DESCRIPTION

Each Anusol-HC® 25 mg Suppository contains 25 mg hydrocortisone acetate in a hydrogenated vegetable oil base. Hydrocortisone acetate is a corticosteroid. Chemically, hydrocortisone acetate is pregn-4-ene-3, 20-dione, 21-(acetyloxy)-11, 17-dihydroxy (11β)- with the following structural formula:

CLINICAL PHARMACOLOGY

In normal subjects, about 26 percent of hydrocortisone acetate is absorbed when the hydrocortisone acetate suppository is applied to the rectum. Absorption of hydrocortisone acetate may vary across abraded or inflamed surfaces.

Topical steroids are primarily effective because of their anti-inflammatory, anti-pruritic and vasoconstrictive action.

INDICATIONS AND USAGE

For use in inflamed hemorrhoids, post-irradiation (factitial) proctitis, as an adjunct in the treatment of chronic ulcerative colitis, cryptitis, other inflammatory conditions of the anorectum, and pruritus ani.

CONTRAINDICATION

Anusol-HC® suppositories are contraindicated in those patients with a history of hypersensitivity to any of the components.

PRECAUTIONS

Do not use unless adequate proctologic examination is made.

If irritation develops, the product should be discontinued and appropriate therapy instituted.

In the presence of an infection, the use of an appropriate antifungal or antibacterial agent should be instituted. If a favorable response does not occur promptly, the corticosteroid should be discontinued until the infection has been adequately controlled.

No long-term studies in animals have been performed to evaluate the carcinogenic potential of corticosteroid suppositories.

Information for Patients:

Staining of fabric may occur with use of the suppository. Precautionary measures are recommended.

Pregnancy:

In laboratory animals, topical steroids have been associated with an increase in the incidence of fetal abnormalities when gestating females have been exposed to rather low dosage levels. There are no adequate and well-controlled studies in pregnant women. Anusol-HC® suppositories should only be used during pregnancy if the potential benefit justifies the risk of the fetus. Drugs of this class should not be used extensively on pregnant patients, in large amounts, or for prolonged periods of time.

Nursing Mothers:

It is not known whether this drug is excreted in human milk, and because many drugs are excreted in human milk and because of the potential for serious adverse reactions in nursing infants from Anusol-HC® suppositories, a decision should be made whether to discontinue nursing or to discontinue the drug, taking into account the importance of the drug to the mother.

ADVERSE REACTIONS

The following local adverse reactions have been reported with corticosteroid suppositories.

1. Burning
2. Itching
3. Irritation
4. Dryness
5. Folliculitis
6. Hypopigmentation
7. Allergic contact dermatitis
8. Secondary infection

To report SUSPECTED ADVERSE REACTIONS, contact Salix Pharmaceuticals at 1-800-321-4576 or FDA at 1-800-FDA-1088 or www.fda.gov/medwatch.

Drug abuse and dependence has not been reported in patients treated with Anusol-HC® suppositories.

OVERDOSAGE

If signs and symptoms of systemic overdosage occur, discontinue use.

DOSAGE AND ADMINISTRATION

Usual Dosage: One suppository in the rectum morning and night for two weeks, in nonspecific proctitis. In more severe cases, one suppository three times daily; or two suppositories twice daily. In factitial proctitis, recommended therapy is six to eight weeks or less, according to response.

HOW SUPPLIED

Anusol-HC® 25 mg Suppositories are white, cylinder shaped, with one end tapered.
NDC 65649-411-12 25 mg 12 suppositories
NDC 65649-411-24 25 mg 24 suppositories

Store at 20° to 25°C (68° to 77°F) [see USP Controlled Room Temperature]. Store away from heat. PROTECT FROM FREEZING.

Distributed by: Salix Pharmaceuticals, a division of Bausch Health US, LLC, Bridgewater, NJ 08807 USA

Anusol-HC is a trademark of Salix Pharmaceuticals, Inc. or its affiliates.

© 2024 Salix Pharmaceuticals, Inc. or its affiliates

OPENING INSTRUCTIONS

Avoid excessive handling of the suppository. It is designed to melt at body temperature.

1. Separate plastic film at top opening and pull downward.

2. Continue pulling downward to almost the full length of the suppository.

3. Gently remove the suppository from the film pocket.

Rev. 07/2024

9520702

PACKAGE LABEL PRINCIPAL DISPLAY PANEL - Carton

NDC 65649-411-12

Rx only

Anusol-HC®

(Hydrocortisone Acetate in a

Hydrogenated Vegetable Oil Base)

25 mg

For rectal use only.

Not for oral use.

12 Suppositories